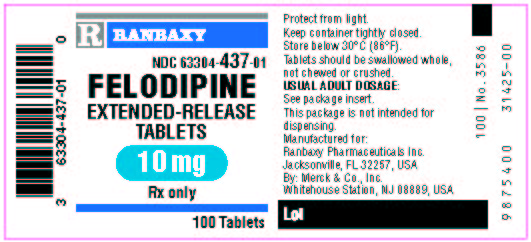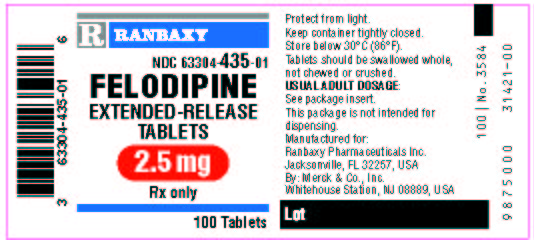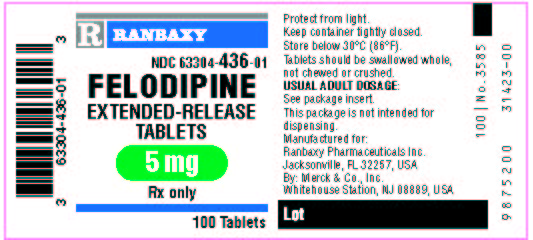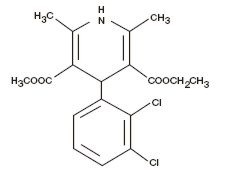 DRUG LABEL: FELODIPINEEXTENDED-RELEASE TABLETS
NDC: 63304-435 | Form: TABLET, EXTENDED RELEASE
Manufacturer: Ranbaxy Pharmaceuticals Inc
Category: prescription | Type: HUMAN PRESCRIPTION DRUG LABEL
Date: 20090909

ACTIVE INGREDIENTS: FELODIPINE 2.5 mg/1 1
INACTIVE INGREDIENTS: HYDROXYPROPYL CELLULOSE; TITANIUM DIOXIDE; LACTOSE; FD&C BLUE NO. 2; SODIUM STEARYL FUMARATE; FERRIC OXIDE YELLOW

Rx only

DESCRIPTION

Felodipine is a calcium antagonist (calcium channel blocker). Felodipine is a dihydropyridine derivative that is chemically described as ± ethyl methyl 4-(2, 3-dichlorophenyl)-1, 4-dihydro-2, 6-dimethyl-3, 5-pyridinedicarboxylate. Its empirical formula is C18H19Cl2NO4 and its structural formula is:

Felodipine is a slightly yellowish, crystalline powder with a molecular weight of 384.26. It is insoluble in water and is freely soluble in dichloromethane and ethanol. Felodipine is a racemic mixture.

Felodipine extended-release tablets provide extended release of felodipine. They are available as tablets containing 2.5 mg, 5 mg, or 10 mg at felodipine for oral administration. In addition to the active ingredient felodipine, the tablets contain the following inactive ingredients: Felodipine extended-release tablets 2.5 mg — hydroxypropyl cellulose, lactose, FD&C Blue 2, sodium stearyl fumarate, titanium dioxide, yellow iron oxide, and other ingredients. Felodipine extended-release tablets 5 mg and 10 mg—cellulose, red and yellow oxide, lactose, polyethylene glycol, sodium stearyl fumarate, titanium dioxide, and other ingredients.

CLINICAL PHARMACOLOGY

Mechanism of Action

Felodipine is a member of the dihydropyridine class of calcium channel antagonists (calcium channel blockers). It reversibly competes with nitrendipine and/or other calcium channel blockers for dihydropyridine binding sites, blocks voltage-dependent Ca^++ currents in vascular smooth muscle and cultured rabbit atrial cells, and blocks potassium-induced contracture of the rat portal vein.

In vitro studies show that the effects of felodipine on contractile processes are selective, with greater effects on vascular smooth muscle than cardiac muscle. Negative inotropic effects can be detected in vitro, but such effects have not been seen in intact animals.

The effect of felodipine on blood pressure is principally a consequence of a dose-related decrease of peripheral vascular resistance in man, with a modest reflex increase in heart rate (see Cardiovascular Effects). With the exception of a mild diuretic effect seen in several animal species and man, the effects of felodipine are accounted for by its effects on peripheral vascular resistance.

Pharmacokinetics and Metabolism

Following oral administration, felodipine is almost completely absorbed and undergoes extensive first-pass metabolism. The systemic bioavailability of felodipine extended-release tablets is approximately 20%. Mean peak concentrations following the administration of felodipine extended-release tablets are reached in 2.5 to 5 hours. Both peak plasma concentration and the area under the plasma concentration time curve (AUC) increase linearly with doses up to 20 mg. Felodipine is greater than 99% bound to plasma proteins.

Following intravenous administration, the plasma concentration of felodipine declined triexponentially with mean disposition half-lives of 4.8 minutes, 1.5 hours, and 9.1 hours. The mean contributions of the three individual phases to the overall AUC were 15, 40, and 45%, respectively, in the order of increasing t1/2.

Following oral administration of the immediate-release formulation, the plasma level of felodipine also declined polyexponentially with a mean terminal t1/2 of 11 to 16 hours. The mean peak and trough steady-state plasma concentrations achieved after 10 mg of the immediate-release formulation given once a day to normal volunteers, were 20 and 0.5 nmol/L, respectively. The trough plasma concentration of felodipine in most individuals was substantially below the concentration needed to effect a half-maximal decline in blood pressure (EC50) [4-6 nmol/L for felodipine], thus precluding once-a-day dosing with the immediate-release formulation.

Following administration of a 10-mg dose of felodipine extended-release tablets, to young, healthy volunteers, mean peak and trough steady-state plasma concentrations of felodipine were 7 and 2 nmol/L, respectively. Corresponding values in hypertensive patients (mean age 64) after a 20-mg dose of felodipine extended-release tablets were 23 and 7 nmol/L. Since the EC50 for felodipine is 4 to 6 nmol/L, a 5- to 10-mg dose of felodipine extended-release tablets in some patients, and a 20-mg dose in others, would be expected to provide an antihypertensive effect that persists for 24 hours (see Cardiovascular Effects below and DOSAGE AND ADMINISTRATION).

The systemic plasma clearance of felodipine in young healthy subjects is about 0.8 L/min, and the apparent volume of distribution is about 10 L/kg.

Following an oral or intravenous dose of ^14C-labeled felodipine in man, about 70% of the dose of radioactivity was recovered in urine and 10% in the feces. A negligible amount of intact felodipine is recovered in the urine and feces (< 0.5%). Six metabolites, which account for 23% of the oral dose, have been identified; none has significant vasodilating activity.

Following administration of felodipine extended-release tablets to hypertensive patients, mean peak plasma concentrations at steady state are about 20% higher than after a single dose. Blood pressure response is correlated with plasma concentrations of felodipine.

The bioavailability of felodipine extended-release tablets is influenced by the presence of food. When administered either with a high fat or carbohydrate diet, Cmax is increased by approximately 60%; AUC is unchanged. When felodipine extended-release tablets were administered after a light meal (orange juice, toast, and cereal), however, there is no effect on felodipine's pharmacokinetics. The bioavailability of felodipine was increased approximately two-fold when taken with grapefruit juice. Orange juice does not appear to modify the kinetics of felodipine extended-release tablets. A similar finding has been seen with other dihydropyridine calcium antagonists, but to a lesser extent than that seen with felodipine.

Geriatric Use

Plasma concentrations of felodipine, after a single dose and at steady state, increase with age. Mean clearance of felodipine in elderly hypertensives (mean age 74) was only 45% of that of young volunteers (mean age 26). At steady state mean AUC for young patients was 39% of that for the elderly. Data for intermediate age ranges suggest that the AUCs fall between the extremes of the young and the elderly.

Hepatic Dysfunction

In patients with hepatic disease, the clearance of felodipine was reduced to about 60% of that seen in normal young volunteers.

Renal impairment does not alter the plasma concentration profile of felodipine; although higher concentrations of the metabolites are present in the plasma due to decreased urinary excretion, these are inactive.

Animal studies have demonstrated that felodipine crosses the blood-brain barrier and the placenta.

Cardiovascular Effects

Following administration of felodipine extended-release tablets, a reduction in blood pressure generally occurs within 2 to 5 hours. During chronic administration, substantial blood pressure control lasts for 24 hours, with trough reductions in diastolic blood pressure approximately 40-50% of peak reductions. The antihypertensive effect is dose dependent and correlates with the plasma concentration of felodipine.

A reflex increase in heart rate frequently occurs during the first week of therapy; this increase attenuates over time. Heart rate increases of 5-10 beats per minute may be seen during chronic dosing. The increase is inhibited by beta-blocking agents.

The P-R interval of the ECG is not affected by felodipine when administered alone or in combination with a beta-blocking agent. Felodipine alone or in combination with a beta-blocking agent has been shown, in clinical and electrophysiologic studies, to have no significant effect on cardiac conduction (P-R, P-Q, and H-V intervals).

In clinical trials in hypertensive patients without clinical evidence of left ventricular dysfunction, no symptoms suggestive of a negative inotropic effect were noted; however, none would be expected in this population (see PRECAUTIONS).

Renal/Endocrine Effects

Renal vascular resistance is decreased by felodipine while glomerular filtration rate remains unchanged. Mild diuresis, natriuresis, and kaliuresis have been observed during the first week of therapy. No significant effects on serum electrolytes were observed during short- and long-term therapy.

In clinical trials in patients with hypertension, increases in plasma noradrenaline levels have been observed.

Clinical Studies

Felodipine produces dose-related decreases in systolic and diastolic blood pressure as demonstrated in six placebo-controlled, dose response studies using either immediate-release or extended-release dosage forms. These studies enrolled over 800 patients on active treatment, at total daily doses ranging from 2.5 to 20 mg. In those studies felodipine was administered either as monotherapy or was added to beta blockers. The results of the 2 studies with felodipine given once daily as monotherapy are shown in the table below:

MEAN REDUCTIONS IN BLOOD PRESSURE (mmHg)*
Dose | N | Systolic/Diastolic Mean Peak Response | Mean Trough Response | Trough/Peak Ratios (%s)
Study 1 (8 weeks)
2.5 mg | 68 | 9.4/4.7 | 2.7/2.5 | 29/53
5 mg | 69 | 9.5/6.3 | 2.4/3.7 | 25/59
10 mg | 67 | 18.0/10.8 | 10.0/6.0 | 56/56
Study 2 (4 weeks)
10 mg | 50 | 5.3/7.2 | 1.5/3.2 | 33/40**
20 mg | 50 | 11.3/10.2 | 4.5/3.2 | 43/34**
* Placebo response subtracted
** Different number of patients available for peak and trough measurements

INDICATIONS AND USAGE

Felodipine extended-release tablets are indicated for the treatment of hypertension. Felodipine extended-release tablets may be used alone or concomitantly with other antihypertensive agents.

CONTRAINDICATIONS

Felodipine extended-release tablets are contraindicated in patients who are hypersensitive to this product.

PRECAUTIONS

General

Hypotension

Felodipine, like other calcium antagonists, may occasionally precipitate significant hypotension and, rarely, syncope. It may lead to reflex tachycardia which in susceptible individuals may precipitate angina pectoris. (See ADVERSE REACTIONS.)

Heart Failure

Although acute hemodynamic studies in a small number of patients with NYHA Class II or III heart failure treated with felodipine have not demonstrated negative inotropic effects, safety in patients with heart failure has not been established. Caution, therefore, should be exercised when using felodipine extended-release tablets in patients with heart failure or compromised ventricular function, particularly in combination with a beta blocker.

Patientswith Impaired Liver Function

Patients with impaired liver function may have elevated plasma concentrations of felodipine and may respond to lower doses of felodipine extended-release tablets; therefore, a starting dose of 2.5 mg once a day is recommended. These patients should have their blood pressure monitored closely during dosage adjustment of felodipine extended-release tablets. (See CLINICAL PHARMACOLOGY and DOSAGE AND ADMINISTRATION.)

Peripheral Edema

Peripheral edema, generally mild and not associated with generalized fluid retention, was the most common adverse event in the clinical trials. The incidence of peripheral edema was both dose and age dependent. Frequency of peripheral edema ranged from about 10% in patients under 50 years of age taking 5 mg daily to about 30% in those over 60 years of age taking 20 mg daily. This adverse effect generally occurs within 2-3 weeks of the initiation of treatment.

Information for Patients

Patients should be instructed to take felodipine extended-release tablets whole and not to crush or chew the tablets. They should be told that mild gingival hyperplasia (gum swelling) has been reported. Good dental hygiene decreases its incidence and severity.

NOTE: As with many other drugs, certain advice to patients being treated with felodipine extended-release tablets are warranted. This information is intended to aid in the safe and effective use of this medication. It is not a disclosure of all possible adverse or intended effects.

Drug Interactions

CYP3A4 Inhibitors

Felodipine is metabolized by CYP3A4. Co-administration of CYP3A4 inhibitors (eg., ketoconazole, itraconazole, erythromycin, grapefruit juice, cimetidine) with felodipine may lead to several-fold increases in the plasma levels of felodipine, either due to an increase in bioavailability or due to a decrease in metabolism. These increases in concentration may lead to increased effects, (lower blood pressure and increased heart rate). These effects have been observed with co-administration of itraconazole (a potent CYP3A4 inhibitor). Caution should be used when CYP3A4 inhibitors are co-administered with felodipine. A conservative approach to dosing felodipine should be taken. The following specific interactions have been reported:

Itraconazole

Co-administration of another extended release formulation of felodipine with itraconazole resulted in approximately 8-fold increase in the AUC, more than 6-fold increase in the Cmax, and 2-fold prolongation in the half-life of felodipine.

Erythromycin

Co-administration of felodipine extended-release tablets with erythromycin resulted in approximately 2.5-fold increase in the AUC and Cmax, and about 2-fold prolongation in the half-life of felodipine.

Grapefruitjuice

Co-administration of felodipine with grapefruit juice resulted in more than 2-fold increase in the AUC and Cmax, but no prolongation in the half-life of felodipine.

Cimetidine

Co-administration of felodipine with cimetidine (a non-specific CYP-450 inhibitor) resulted in an increase of approximately 50% in the AUC and the Cmax, of felodipine.

Beta-Blocking Agents

A pharmacokinetic study of felodipine in conjunction with metoprolol demonstrated no significant effects on the pharmacokinetics of felodipine. The AUC and Cmax of metoprolol, however, were increased approximately 31 and 38%, respectively. In controlled clinical trials, however, beta blockers including metoprolol were concurrently administered with felodipine and were well tolerated.

Digoxin

When given concomitantly with felodipine extended-release tablets the pharmacokinetics of digoxin in patients with heart failure were not significantly altered.

Anticonvulsants

In a pharmacokinetic study, maximum plasma concentrations of felodipine were considerably lower in epileptic patients on long-term anticonvulsant therapy (eg, phenytoin. carbamazepine, or phenobarbital) than in healthy volunteers. In such patients, the mean area under the felodipine plasma concentration-time curve was also reduced to approximately 6% of that observed in healthy volunteers. Since a clinically significant interaction may be anticipated, alternative antihypertensive therapy should be considered in these patients.

Tacrolimus

Felodipine may increase the blood concentration of tacrolimus. When given concomitantly with felodipine, the tacrolimus blood concentration should be followed and the tacrolimus dose may need to be adjusted.

Other Concomitant Therapy

In healthy subjects there were no clinically significant interactions when felodipine was given concomitantly with indomethacin or spironolactone.

Interactionwith Food

See CLINICAL PHARMACOLOGY, Pharmacokinetics and Metabolism.

Carcinogenesis, Mutagenesis, Impairment of Fertility

In a 2-year carcinogenicity study in rats fed felodipine at doses of 7.7, 23.1 or 69.3 mg/kg/day (up to 61 times** the maximum recommended human dose on a mg/m^2 basis), a dose-related increase in the incidence of benign interstitial cell tumors of the testes (Leydig cell tumors) was observed in treated male rats. These tumors were not observed in a similar study in mice at doses up to 138.6 mg/kg/day (61 times** the maximum recommended human dose on a mg/m^2 basis). Felodipine, at the doses employed in the 2-year rat study, has been shown to lower testicular testosterone and to produce a corresponding increase in serum luteinizing hormone in rats. The Leydig cell tumor development is possibly secondary to these hormonal effects which have not been observed in man.

In this same rat study a dose-related increase in the incidence of focal squamous cell hyperplasia compared to control was observed in the esophageal groove of male and female rats in all dose groups. No other drug-related esophageal or gastric pathology was observed in the rats or with chronic administration in mice and dogs. The latter species, like man, has no anatomical structure comparable to the esophageal groove.

Felodipine was not carcinogenic when fed to mice at doses up to 138.6 mg/kg/day (61 times** the maximum recommended human dose on a mg/m^2 basis) for periods of up to 80 weeks in males and 99 weeks in females.

Felodipine did not display any mutagenic activity in vitro in the Ames microbial mutagenicity test or in the mouse lymphoma forward mutation assay. No clastogenic potential was seen in vivo in the mouse micronucleus test at oral doses up to 2500 mg/kg (1100 times** the maximum recommended human dose on a mg/m^2 basis) or in vitro in a human lymphocyte chromosome aberration assay.

A fertility study in which male and female rats were administered doses of 3.8, 9.6 or 26.9 mg/kg/day (up to 24 times** the maximum recommended human dose on a mg/m^2 basis) showed no significant effect of felodipine on reproductive performance.

Pregnancy

Pregnancy Category C

Teratogenic Effects

Studies in pregnant rabbits administered doses of 0.46, 1.2, 2.3, and 4.6 mg/kg/day (from 0.8 to 8 times** the maximum recommended human dose on a mg/m^2 basis) showed digital anomalies consisting of reduction in size and degree of ossification of the terminal phalanges in the fetuses. The frequency and severity of the changes appeared dose related and were noted even at the lowest dose. These changes have been shown to occur with other members of the dihydropyridine class and are possibly a result of compromised uterine blood flow. Similar fetal anomalies were not observed in rats given felodipine.

In a teratology study in cynomolgus monkeys, no reduction in the size of the terminal phalanges was observed, but an abnormal position of the distal phalanges was noted in about 40% of the fetuses.

Nonteratogenic Effects

A prolongation of parturition with difficult labor and an increased frequency of fetal and early postnatal deaths were observed in rats administered doses of 9.6 mg/kg/day (8 times** the maximum human dose on a mg/m^2 basis) and above.

Significant enlargement of the mammary glands, in excess of the normal enlargement for pregnant rabbits, was found with doses greater than or equal to 1.2 mg/kg/day (2.1 times the maximum human dose on a mg/m^2 basis). This effect occurred only in pregnant rabbits and regressed during lactation. Similar changes in the mammary glands were not observed in rats or monkeys.

There are no adequate and well-controlled studies in pregnant women. If felodipine is used during pregnancy, or if the patient becomes pregnant while taking this drug, she should be apprised of the potential hazard to the fetus, possible digital anomalies of the infant, and the potential effects of felodipine on labor and delivery and on the mammary glands of pregnant females.

[** Based on patient weight at 50 kg]

Nursing Mothers

It is not known whether this drug is secreted in human milk and because of the potential for serious adverse reactions from felodipine in the infant, a decision should be made whether to discontinue nursing or to discontinue the drug, taking into account the importance of the drug to the mother.

Pediatric Use

Safety and effectiveness in pediatric patients have not been established.

Geriatric Use

Clinical studies of felodipine did not include sufficient numbers of subjects aged 65 and over to determine whether they respond differently from younger subjects. Other reported clinical experience has not identified differences in responses between the elderly and younger patients. Pharmacokinetics, however, indicate that the availability of felodipine is increased in older patients (see CLINICAL PHARMACOLOGY, Geriatric Use). In general, dose selection for an elderly patient should be cautious, usually starting at the low end of the dosing range, reflecting the greater frequency of decreased hepatic, renal, or cardiac function, and of concomitant disease or other drug therapy.

ADVERSE REACTIONS

In controlled studies in the United States and overseas, approximately 3000 patients were treated with felodipine as either the extended-release or the immediate-release formulation.

The most common clinical adverse events reported with felodipine extended-release tablets administered as monotherapy at the recommended dosage range of 2.5 mg to 10 mg once a day were peripheral edema and headache. Peripheral edema was generally mild, but it was age and dose related and resulted in discontinuation of therapy in about 3% of the enrolled patients. Discontinuation of therapy due to any clinical adverse event occurred in about 6% of the patients receiving felodipine extended-release tablets, principally for peripheral edema, headache, or flushing.

Adverse events that occurred with an incidence of 1.5% or greater at any of the recommended doses of 2.5 mg to 10 mg once a day (felodipine extended-release tablets N = 861; Placebo, N = 334), without regard to causality, are compared to placebo and are listed by dose in the table below. These events are reported from controlled clinical trials with patients who were randomized to a fixed dose of felodipine extended-release tablets or titrated from an initial dose of 2.5 mg or 5 mg once a day. A dose of 20 mg once a day has been evaluated in some clinical studies. Although the antihypertensive effect of felodipine extended-release tablets is increased at 20 mg once a day, there is a disproportionate increase in adverse events, especially those associated with vasodilatory effects (see DOSAGE AND ADMINISTRATION).

Percent of Patients with Adverse Events in Controlled Trials* of Felodipine Extended-Release Tablets (N = 861) as Monotherapy without Regard to Causality (Incidence of discontinuations shown in parentheses)
Body System | Placebo | 2.5 mg | 5 mg | 10 mg
Adverse Events | N = 334 | N = 255 | N = 581 | N = 408
Body as a Whole
Peripheral Edema | 3.3 (0.0) | 2.0 (0.0) | 8.8 (2.2) | 17.4 (2.5)
Asthenia | 3.3 (0.0) | 3.9 (0.0) | 3.3 (0.0) | 2.2 (0.0)
Warm Sensation | 0.0 (0.0) | 0.0 (0.0) | 0.9 (0.2) | 1.5 (0.0)
Cardiovascular
Palpitation | 2.4 (0.0) | 0.4 (0.0) | 1.4 (0.3) | 2.5 (0.5)
Digestive
Nausea | 1.5 (0.9) | 1.2 (0.0) | 1.7 (0.3) | 1.0 (0.7)
Dyspepsia | 1.2 (0.0) | 3.9 (0.0) | 0.7 (0.0) | 0.5 (0.0)
Constipation | 0.9 (0.0) | 1.2 (0.0) | 0.3 (0.0) | 1.5 (0.2)
Nervous
Headache | 10.2 (0.9) | 10.6 (0.4) | 11.0 (1.7) | 14.7 (2.0)
Dizziness | 2.7 (0.3) | 2.7 (0.0) | 3.6 (0.5) | 3.7 (0.5)
Paresthesia | 1.5 (0.3) | 1.6 (0.0) | 1.2 (0.0) | 1.2 (0.2)
Respiratory
Upper Respiratory Infection | 1.8 (0.0) | 3.9 (0.0) | 1.9 (0.0) | 0.7 (0.0)
Cough | 0.3 (0.0) | 0.8 (0.0) | 1.2 (0.0) | 1.7 (0.0)
Rhinorrhea | 0.0 (0.0) | 1.6 (0.0) | 0.2 (0.0) | 0.2 (0.0)
Sneezing | 0.0 (0.0) | 1.6 (0.0) | 0.0 (0.0) | 0.0 (0.0)
Skin
Rash | 0.9 (0.0) | 2.0 (0.0) | 0.2 (0.0) | 0.2 (0.0)
Flushing | 0.9 (0.3) | 3.9 (0.0) | 5.3 (0.7) | 6.9 (1.2)
*Patients in titration studies may have been exposed to more than one dose level of felodipine extended-release tablets.

Adverse events that occurred in 0.5 up to 1.5% of patients who received felodipine extended-release tablets in all controlled clinical trials at the recommended dosage range of 2.5 mg to 10 mg once a day, and serious adverse events that occurred at a lower rate, or events reported during marketing experience (those lower rate events are in italics) are listed below. These events are listed in order of decreasing severity within each category, and the relationship of these events to administration of felodipine extended-release tablets is uncertain: Body as a Whole: Chest pain, facial edema, flu-like illness; Cardiovascular: Myocardial infarction, hypotension, syncope, angina pectoris, arrhythmia, tachycardia, premature beats; Digestive: Abdominal pain, diarrhea, vomiting, dry mouth, flatulence, acid regurgitation; Endocrine: Gynecomastia; Hematologic: Anemia; Metabolic: ALT (SGPT) increased; Musculoskeletal: Arthralgia, back pain, leg pain, foot pain, muscle cramps, myalgia, arm pain, knee pain, hip pain; Nervous/Psychiatric: Insomnia, depression, anxiety disorders, irritability, nervousness, somnolence, decreased libido; Respiratory: Dyspnea, pharyngitis, bronchitis, influenza, sinusitis, epistaxis, respiratory infection; Skin: Angioedema, contusion, erythema, urticaria, leukocytoclastic vasculitis; Special Senses: Visual disturbances; Urogenital: Impotence, urinary frequency, urinary urgency, dysuria, polyuria.

Gingival Hyperplasia — Gingival hyperplasia, usually mild, occurred in < 0.5% of patients in controlled studies. This condition may be avoided or may regress with improved dental hygiene. (See PRECAUTIONS, Information for Patients.)

Clinical Laboratory Test Findings

Serum Electrolytes— No significant effects on serum electrolytes were observed during short- and long-term therapy (see CLINICAL PHARMACOLOGY, Renal/Endocrine Effects).

Serum Glucose— No significant effects on fasting serum glucose were observed in patients treated with felodipine extended-release tablets in the U.S. controlled study.

Liver Enzymes— 1 of 2 episodes of elevated serum transaminases decreased once drug was discontinued in clinical studies; no follow-up was available for the other patient.

OVERDOSAGE

Oral doses of 240 mg/kg and 264 mg/kg in male and female mice, respectively, and 2390 mg/kg and 2250 mg/kg in male and female rats, respectively, caused significant lethality.

In a suicide attempt, one patient took 150 mg felodipine together with 15 tablets each of atenolol and spironolactone and 20 tablets of nitrazepam. The patient's blood pressure and heart rate were normal on admission to hospital; he subsequently recovered without significant sequelae.

Overdosage might be expected to cause excessive peripheral vasodilation with marked hypotension and possibly bradycardia.

If severe hypotension occurs, symptomatic treatment should be instituted. The patient should be placed supine with the legs elevated. The administration of intravenous fluids may be useful to treat hypotension due to overdosage with calcium antagonists. In case of accompanying bradycardia, atropine (0.5-1 mg) should be administered intravenously. Sympathomimetic drugs may also be given if the physician feels they are warranted.

It has not been established whether felodipine can be removed from the circulation by hemodialysis.

To obtain up-to-date information about the treatment of overdose, consult your Regional Poison-Control Center. Telephone numbers of certified poison-control centers are listed in the Physicians' Desk Reference (PDR). In managing overdose, consider the possibilities of multiple-drug overdoses, drug-drug interactions, and unusual drug kinetics in your patient.

DOSAGE AND ADMINISTRATION

The recommended starting dose is 5 mg once a day. Depending on the patient's response, the dosage can be decreased to 2.5 mg or increased to 10 mg once a day. These adjustments should occur generally at intervals of not less than 2 weeks. The recommended dosage range is 2.5 - 10 mg once daily. In clinical trials, doses above 10 mg daily showed an increased blood pressure response but a large increase in the rate of peripheral edema and other vasodilatory adverse events (see ADVERSE REACTIONS). Modification of the recommended dosage is usually not required in patients with renal impairment.

Felodipine extended-release tablets should regularly be taken either without food or with a light meal (see CLINICAL PHARMACOLOGY, Pharmacokinetics and Metabolism). Felodipine extended-release tablets should be swallowed whole and not crushed or chewed.

Geriatric Use

Patients over 65 years of age are likely to develop higher plasma concentrations of felodipine (see CLINICAL PHARMACOLOGY). In general, dose selection for an elderly patient should be cautious, usually starting at the low end of the dosing range (2.5 mg daily). Elderly patients should have their blood pressure closely monitored during any dosage adjustment.

Patients with impaired liver function may have elevated plasma concentrations of felodipine and may respond to lower doses of felodipine extended-release tablets; therefore, patients should have their blood pressure monitored closely during dosage adjustment of felodipine extended-release tablets (see CLINICAL PHARMACOLOGY).

HOW SUPPLIED

No.3584 — Felodipine extended-release tablets, 2.5 mg, are sage green, round convex tablets, with code 450 on one side and PLENDIL on the other. They are supplied as follows:

NDC 63304-435-01 bottles of 100

No.3585 — Felodipine extended-release tablets, 5 mg, are light red-brown, round convex tablets, with code 451 on one side and PLENDIL on the other. They are supplied as follows:

NDC 63304-436-01 bottles of 100

No.3586 — Felodipine extended-release tablets, 10 mg, are red-brown, round convex tablets, with code 452 on one side and PLENDIL on the other. They are supplied as follows:

NDC 63304-437-01 bottles of 100

Storage

Store below 30°C (86°F). Keep container tightly closed. Protect from light.

PLENDIL is a trademark of the Astrazeneca group of companies

© Astrazeneca 2008

Manufactured for:

Ranbaxy Pharmaceuticals Inc.

Jacksonville, FL 32257, USA

By: Merck & Co., Inc

Whitehouse Station, NJ, 08889, USA

9874900

31427-00 Rev. 07/08

PACKAGE LABEL PRINCIPAL DISPLAY PANEL

2.5 mg_- 100’S BOTTLE LABEL

5 mg - 100’S BOTTLE LABEL
10 mg - 100’S BOTTLE LABEL